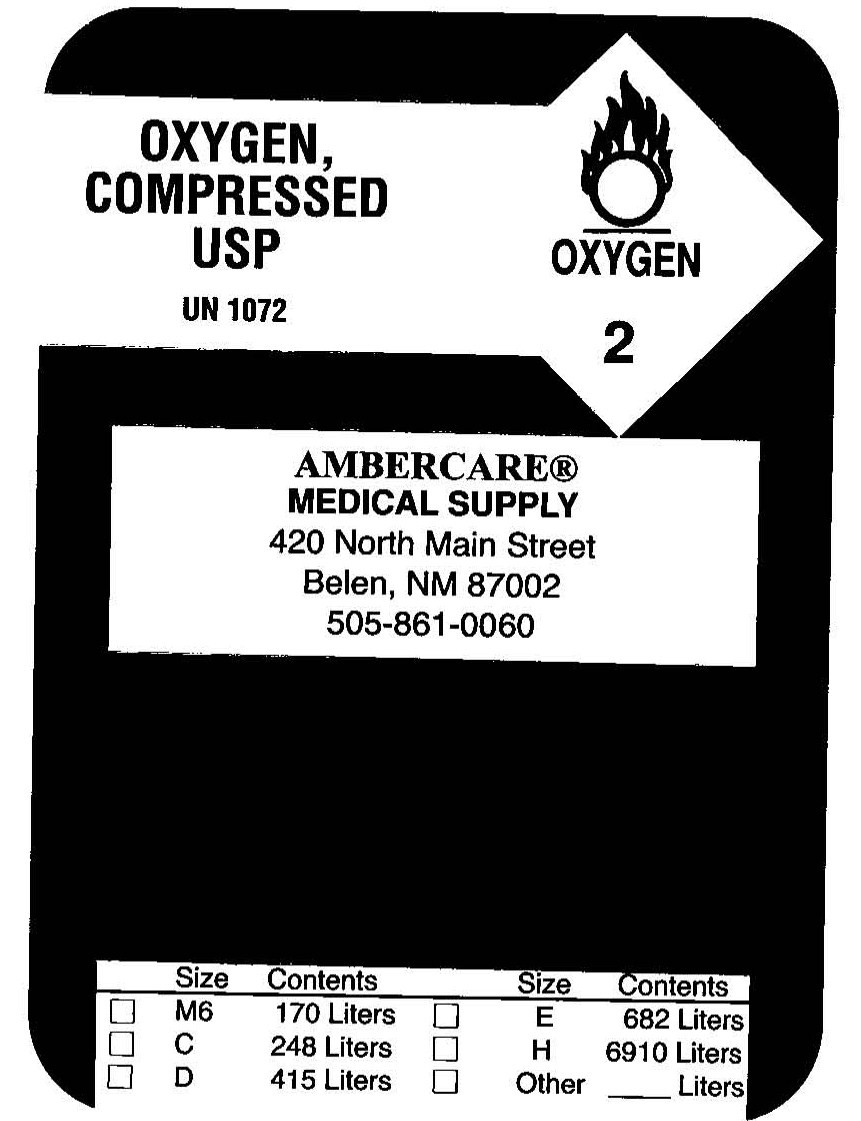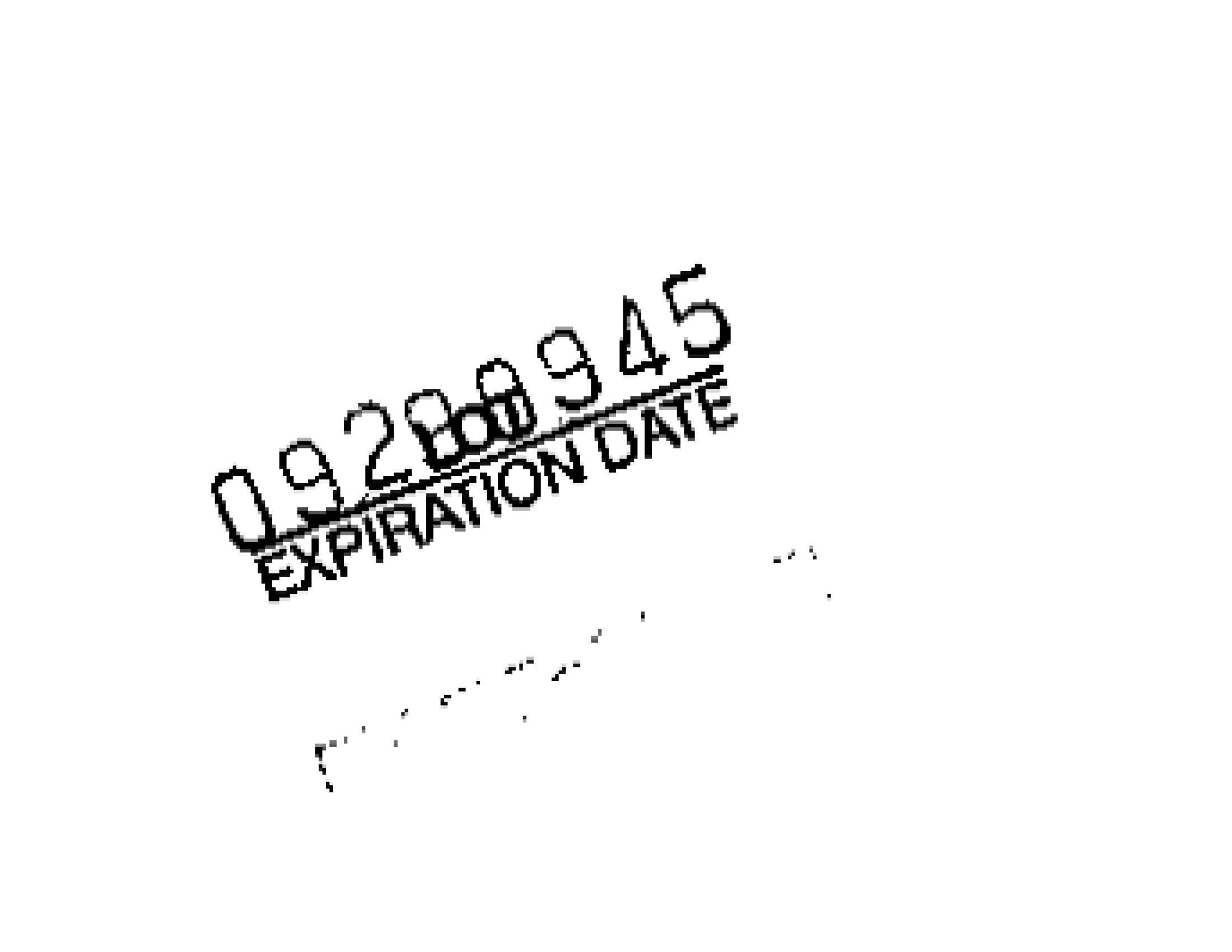 DRUG LABEL: Oxygen
NDC: 64696-1968 | Form: GAS
Manufacturer: Ambercare Medical Supply Co. 
Category: prescription | Type: HUMAN PRESCRIPTION DRUG LABEL
Date: 20100105

ACTIVE INGREDIENTS: Oxygen 99 L/100 L

Oxygen